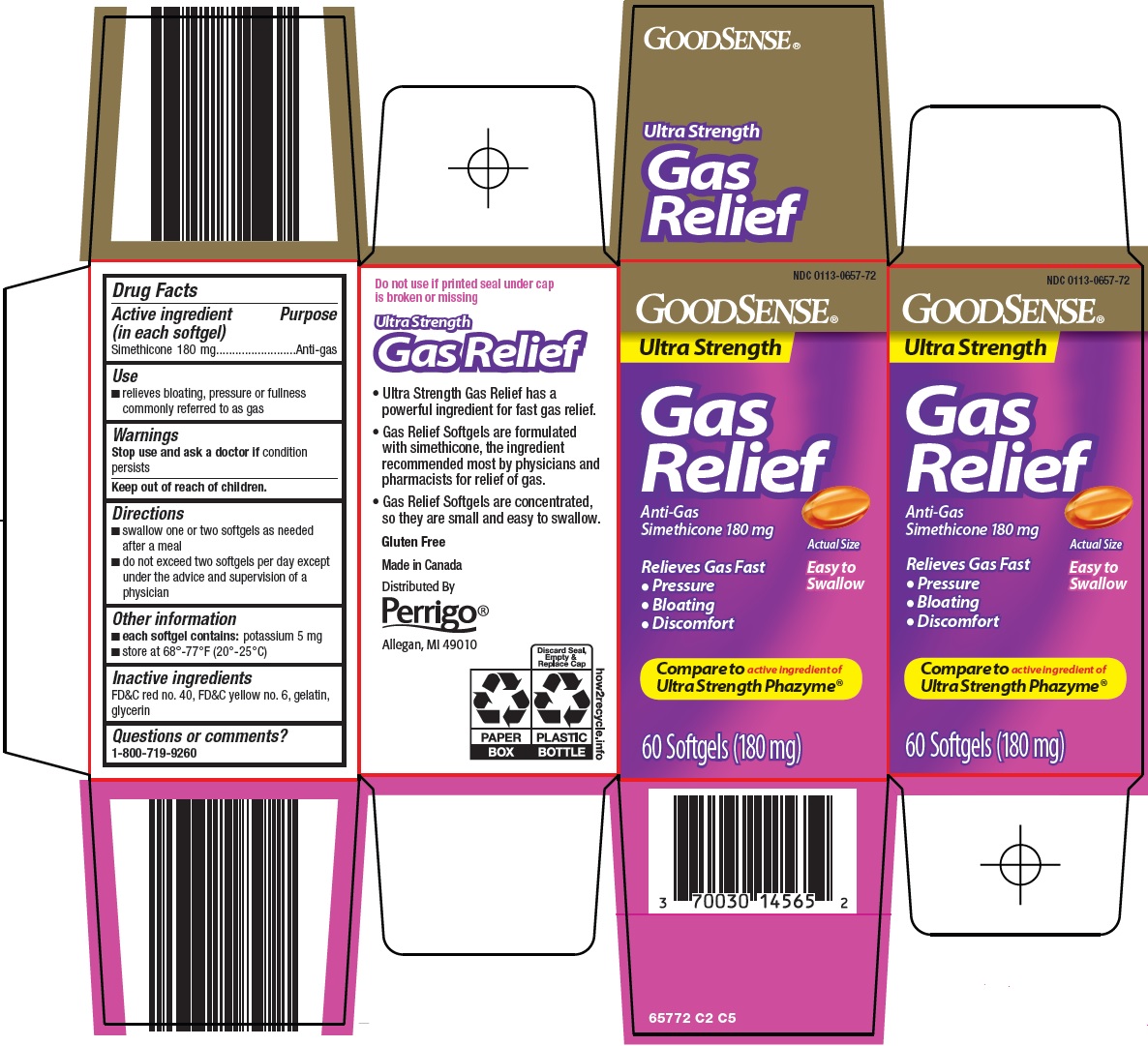 DRUG LABEL: good sense gas relief
NDC: 0113-0657 | Form: CAPSULE, LIQUID FILLED
Manufacturer: L. Perrigo Company
Category: otc | Type: HUMAN OTC DRUG LABEL
Date: 20240930

ACTIVE INGREDIENTS: DIMETHICONE 180 mg/1 1
INACTIVE INGREDIENTS: SILICON DIOXIDE; FD&C RED NO. 40; FD&C YELLOW NO. 6; GELATIN, UNSPECIFIED; GLYCERIN

Perrigo Gas Relief Drug Facts

Active ingredient (in each softgel)

Simethicone 180 mg

Purpose

Anti-gas

Use

- relieves bloating, pressure or fullness commonly referred to as gas

Warnings

Stop use and ask a doctor if

condition persists

Directions

- swallow one or two softgels as needed after a meal
- do not exceed two softgels per day except under the advice and supervision of a physician

Other information

- each softgel contains: potassium 5 mg
- store at 68°-77°F (20°-25°C)

Inactive ingredients

FD&C red no. 40, FD&C yellow no. 6, gelatin, glycerin

Questions or comments?

1-800-719-9260

Principal Display Panel

GOODSENSE®

Ultra Strength

Gas Relief

Anti-Gas

Simethicone 180 mg

Actual Size

Relieves Gas Fast

● Pressure

● Bloating

● Discomfort

Easy to Swallow

Compare to active ingredient of Ultra Strength Phazyme®

60 Softgels (180 mg)